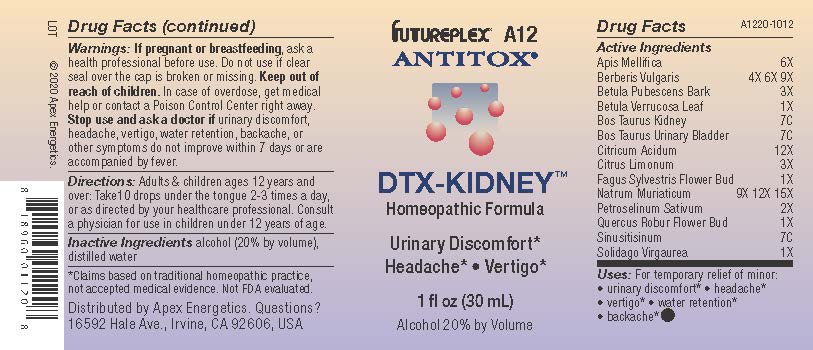 DRUG LABEL: A12
NDC: 63479-0112 | Form: SOLUTION/ DROPS
Manufacturer: Apex Energetics Inc.
Category: homeopathic | Type: HUMAN OTC DRUG LABEL
Date: 20240108

ACTIVE INGREDIENTS: PETROSELINUM CRISPUM 2 [hp_X]/1 mL; SOLIDAGO VIRGAUREA FLOWERING TOP 1 [hp_X]/1 mL; BETULA PUBESCENS BARK 3 [hp_X]/1 mL; BETULA PENDULA LEAF 1 [hp_X]/1 mL; BEEF KIDNEY 7 [hp_C]/1 mL; FAGUS SYLVATICA FLOWER BUD 1 [hp_X]/1 mL; BERBERIS VULGARIS ROOT BARK 9 [hp_X]/1 mL; BOS TAURUS URINARY BLADDER 7 [hp_C]/1 mL; ANHYDROUS CITRIC ACID 12 [hp_X]/1 mL; LEMON JUICE 3 [hp_X]/1 mL; QUERCUS ROBUR FLOWER BUD 1 [hp_X]/1 mL; SINUSITISINUM 7 [hp_C]/1 mL; APIS MELLIFERA 6 [hp_X]/1 mL; SODIUM CHLORIDE 15 [hp_X]/1 mL
INACTIVE INGREDIENTS: ALCOHOL; WATER

A12

Active Ingredients
Apis Mellifica | 6X
Berberis Vulgaris | 4X 6X 9X
Betula Pubescens Bark | 3X
Betula Verrucosa Leaf | 1X
Bos Taurus Kidney | 7C
Bos Taurus Urinary Bladder | 7C
Citricum Acidum | 12X
Citrus Limonum | 3X
Fagus Sylvestris Flower Bud | 1X
Natrum Muriaticum | 9X 12X 15X
Petroselinum Sativum | 2X
Quercus Robur Flower Bud | 1X
Sinusitisinum | 7C
Solidago Virgaurea | 1X

INDICATIONS AND USAGE

Uses:

For temporary relief of minor:

urinary discomfort*

headache*

vertigo*

water retention*

backache*

*Claims based on traditional homeopathic practice, not accepted medical evidence. Not FDA evaluated.

Warnings:

PREGNANCY OR BREAST FEEDING

If pregnant or breastfeeding, ask a health professional before use.

Do not use if clear seal over the cap is broken or missing.

Keep out of reach of children. In case of overdose, get medical help or contact a Poison Control Center right away.

Stop use and ask a doctor if urinary discomfort, headache, vertigo, water retention, backache, or other symptoms do not improve within 7 days or are accompanied by fever.

Directions:

Adults & children ages 12 years and over: Take10 drops under the tongue 2-3 times a day, or as directed by your healthcare professional. Consult a physician for use in children under 12 years of age.

Inactive Ingredients

alcohol (20% by volume), distilled water

Distributed by Apex Energetics. Questions?

16592 Hale Ave., Irvine, CA 92606, USA

PACKAGE LABEL

FUTUREPLEX® A12

ANTITOX®

DTX-KIDNEY™

Homeopathic Formula

Urinary Discomfort*

Headache* Vertigo*

1 fl oz (30 mL)

Alcohol 20% by Volume